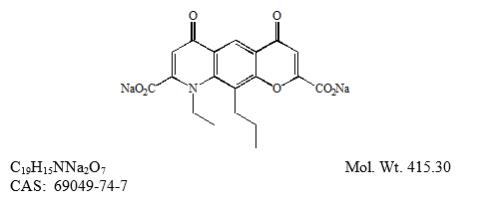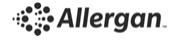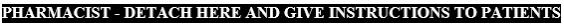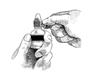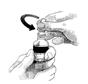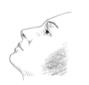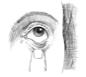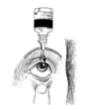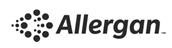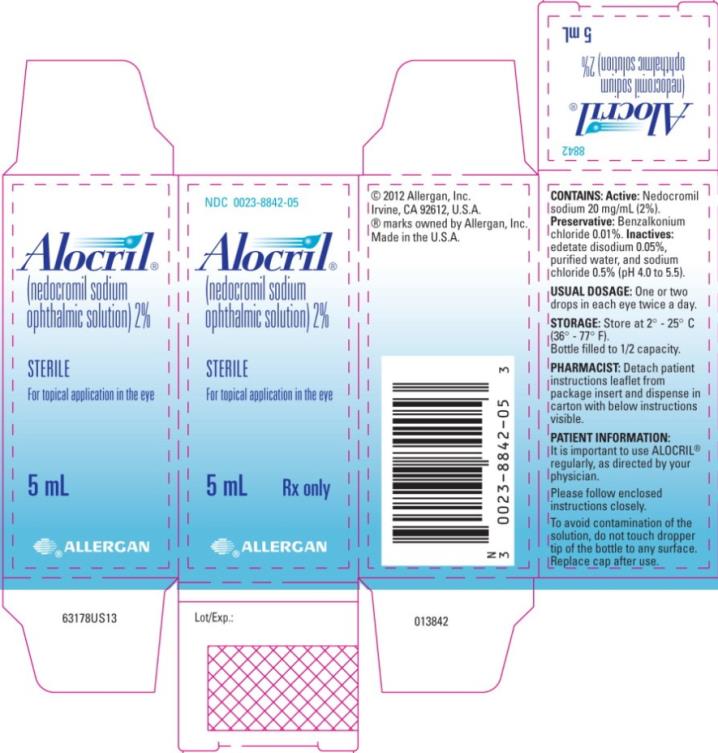 DRUG LABEL: ALOCRIL
NDC: 0023-8842 | Form: SOLUTION/ DROPS
Manufacturer: Allergan, Inc.
Category: prescription | Type: HUMAN PRESCRIPTION DRUG LABEL
Date: 20180601

ACTIVE INGREDIENTS: NEDOCROMIL SODIUM 20 mg/1 mL
INACTIVE INGREDIENTS: EDETATE DISODIUM; WATER; SODIUM CHLORIDE; BENZALKONIUM CHLORIDE

ALOCRIL® (nedocromil sodium ophthalmic solution) 2%
sterile

DESCRIPTION

ALOCRIL® (nedocromil sodium ophthalmic solution) 2% is a clear, yellow, sterile solution for topical ophthalmic use.

Nedocromil sodium is represented by the following structural formula:

Chemical Name: 4H-Pyrano[3,2-g]quinoline-2,8-dicarboxylic acid, 9-ethyl-6,9-dihydro-4,6-dioxo-10-propyl-, disodium salt.

Each mL contains: Active: Nedocromil sodium 20 mg/mL (2%); Preservative: Benzalkonium chloride 0.01%; Inactives: Edetate disodium 0.05%, purified water, and sodium chloride 0.5%. It has a pH range of 4.0 to 5.5 and an osmolality range of 270 to 330 mOsm/kg.

CLINICAL PHARMACOLOGY

Nedocromil sodium is a mast cell stabilizer. Nedocromil sodium inhibits the release of mediators from cells involved in hypersensitivity reactions. Decreased chemotaxis and decreased activation of eosinophils have also been demonstrated.

In vitro studies with adult human bronchoalveolar cells showed that nedocromil sodium inhibits histamine release from a population of mast cells having been defined as belonging to the mucosal sub type and inhibits beta-glucuronidase release from macrophages.

Pharmacokinetics and Bioavailability

Nedocromil sodium exhibits low systemic absorption. When administered as a 2% ophthalmic solution in adult human volunteers, less than 4% of the total dose was systemically absorbed following multiple dosing. Absorption is mainly through the nasolacrimal duct rather than through the conjunctiva. It is not metabolized and is eliminated primarily unchanged in urine (70%) and feces (30%).

INDICATIONS AND USAGE

ALOCRIL® ophthalmic solution is indicated for the treatment of itching associated with allergic conjunctivitis.

CONTRAINDICATIONS

ALOCRIL® ophthalmic solution is contraindicated in those patients who have shown hypersensitivity to nedocromil sodium or to any of the other ingredients.

PRECAUTIONS

Information for Patients

Patients should be advised to follow the patient instructions listed on the Information for Patients sheet.

Users of contact lenses should refrain from wearing lenses while exhibiting the signs and symptoms of allergic conjunctivitis.

Patients should be instructed to avoid allowing the tip of the dispensing container to contact the eye, surrounding structures, fingers, or any other surface in order to avoid contamination of the solution by common bacteria known to cause ocular infections. Serious damage to the eye and subsequent loss of vision may result from using contaminated solutions.

Carcinogenesis, Mutagenesis, and Impairment of Fertility

A two-year inhalation carcinogenicity study of nedocromil sodium at a dose of 24 mg/kg/day (approximately 400 times the maximum recommended human daily ocular dose on a mg/kg basis) in Wistar rats showed no carcinogenic potential.

Nedocromil sodium showed no mutagenic potential in the Ames Salmonella/microsome plate assay, mitotic gene conversion in Saccharomyces cerevisiae, mouse lymphoma forward mutation and mouse micronucleus assays.

Reproduction and fertility studies in mice and rats showed no effects on male and female fertility at a subcutaneous dose of 100 mg/kg/day (more than 1600 times the maximum recommended human daily ocular dose).

Pregnancy

Teratogenic Effects

Reproduction studies performed in mice, rats and rabbits using a subcutaneous dose of 100 mg/kg/day (more than 1600 times the maximum human daily ocular dose on a mg/kg basis) revealed no evidence of teratogenicity or harm to the fetus due to nedocromil sodium. There are, however, no adequate and well-controlled studies in pregnant women. Because animal reproduction studies are not always predictive of human response, ALOCRIL® ophthalmic solution should be used during pregnancy only if clearly needed.

Nursing Mothers

After intravenous administration to lactating rats, nedocromil was excreted in milk. It is not known whether this drug is excreted in human milk. Because many drugs are excreted in human milk, caution should be exercised when ALOCRIL® ophthalmic solution is administered to a nursing woman.

Pediatric Use

Safety and effectiveness in children below the age of 3 years have not been established.

Geriatric Use

No overall differences in safety or effectiveness have been observed between elderly and younger patients.

ADVERSE REACTIONS

The most frequently reported adverse experience was headache (~40%).

Ocular burning, irritation and stinging, unpleasant taste, and nasal congestion have been reported to occur in 10 – 30% of patients. Other events occurring between 1 – 10% included asthma, conjunctivitis, eye redness, photophobia, and rhinitis.

Some of these events were similar to the underlying ocular disease being studied.

DOSAGE AND ADMINISTRATION

The recommended dosage is one or two drops in each eye twice a day. ALOCRIL® ophthalmic solution should be used at regular intervals.

Treatment should be continued throughout the period of exposure (i.e., until the pollen season is over or until exposure to the offending allergen is terminated), even when symptoms are absent.

HOW SUPPLIED

ALOCRIL® (nedocromil sodium ophthalmic solution) 2% is supplied sterile in opaque white LDPE plastic bottles with dropper tips and white high impact polystyrene (HIPS) caps as follows:

5 mL in 10 mL bottle NDC 0023-8842-05

Storage:

Store at 2º–25º C (36º–77º F).

Rx only

Revised: 06/2018

Distributed by: Allergan USA, Inc.

Madison, NJ 07940

© 2018 Allergan. All rights reserved.

All trademarks are the property of their respective owners.

v1.0USPI8842

Information for the Patient

ALOCRIL®

(nedocromil sodium ophthalmic solution) 2%

sterile

It is important to use ALOCRIL® ophthalmic solution regularly, as directed by your physician.

1. Thoroughly wash your hands.

2. Remove safety seal (Figure 1).

3. Remove cap (Figure 2).

4. Sit or stand comfortably, with your head tilted back (Figure 3).

5. Open eyes, look up, and draw the lower lid of your eye down gently with your index finger (Figure 4).

6. Hold the ALOCRIL® bottle upside down. Place tip as close as possible to the lower eyelid without touching the tip to the eye, and gently squeeze out the prescribed number of drops (Figure 5).

7. Do not touch the eye or eyelid with the bottle tip.

8. Blink a few times to make sure the eye is covered with the solution.

9. Close your eye and remove any excess solution with a clean tissue.

10. Repeat process in the other eye.

SPECIAL TIPS

1. Avoid placing ALOCRIL® ophthalmic solution directly on the cornea (the area just over the pupil), because it is especially sensitive. You will find the administration of eye drops more comfortable if you place the drops just inside the lower eyelid as shown in Figure 5 on the previous page.

2. To avoid contamination of the solution, do not touch dropper tip to the eye, fingers, or any other surface. Replace bottle cap after use. It is recommended that any remaining contents be discarded after treatment period prescribed by your physician.

3. Store at 2º–25º C (36º–77º F). Store in original carton.

4. Keep bottle tightly closed and out of the reach of children.

5. Do not use with any other ocular medication unless directed by your physician. Do not wear contact lenses during treatment with ALOCRIL® ophthalmic solution.

Figure 1

Figure 2

Figure 3

Figure 4

Figure 5

Distributed by: Allergan USA, Inc.

Madison, NJ 07940

© 2018 Allergan. All rights reserved.

All trademarks are the property of their respective owners.

v1.0PPI8842

PRINCIPAL DISPLAY PANEL

NDC 0023-8842-05
ALOCRIL®
(nedocromil sodium
ophthalmic solution) 2%
sterile
For topical application in the eye
5 mL